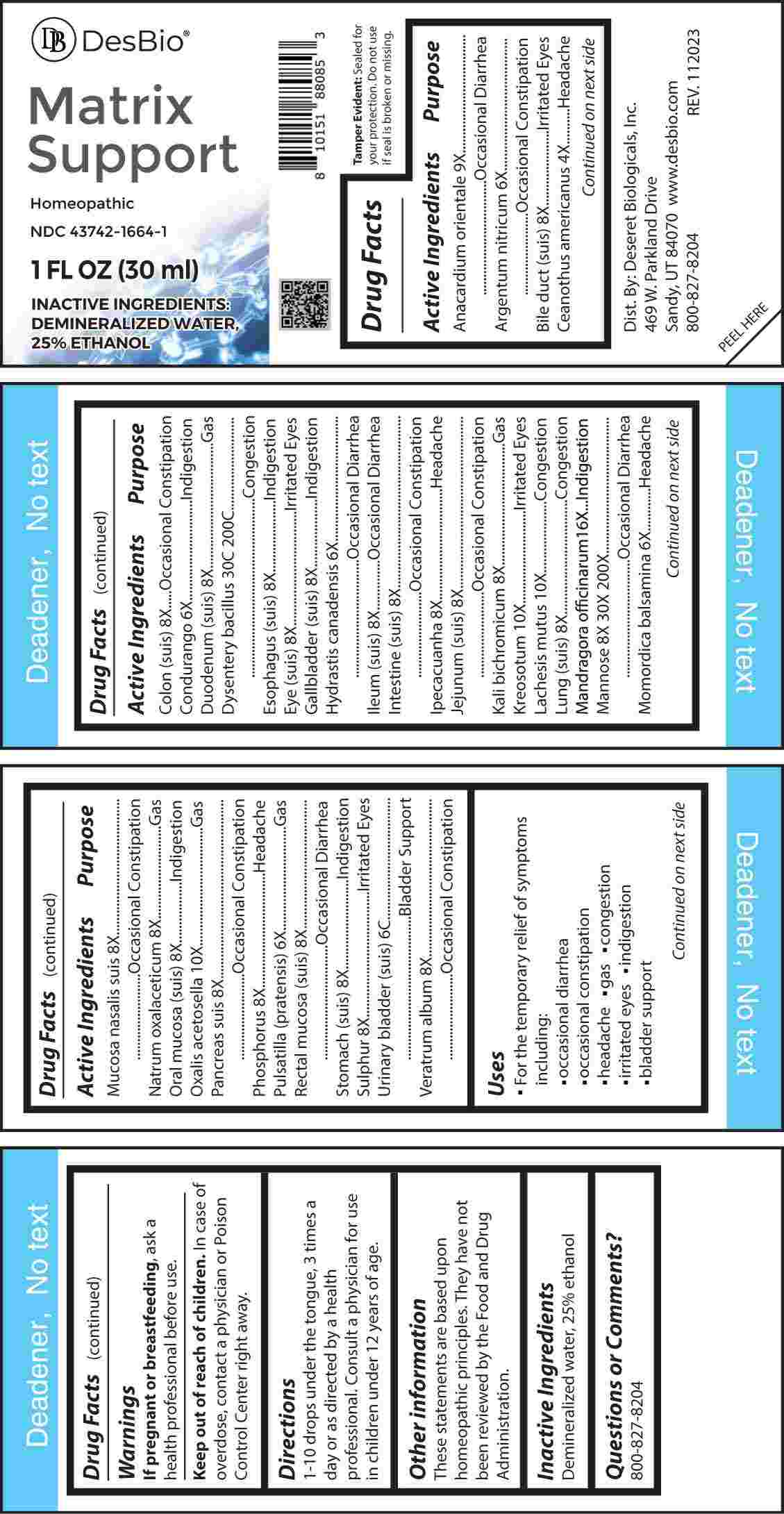 DRUG LABEL: Matrix Support
NDC: 43742-1664 | Form: LIQUID
Manufacturer: Deseret Biologicals, Inc.
Category: homeopathic | Type: HUMAN OTC DRUG LABEL
Date: 20240313

ACTIVE INGREDIENTS: CEANOTHUS AMERICANUS LEAF 4 [hp_X]/1 mL; SILVER NITRATE 6 [hp_X]/1 mL; MARSDENIA CONDURANGO BARK 6 [hp_X]/1 mL; GOLDENSEAL 6 [hp_X]/1 mL; MOMORDICA BALSAMINA IMMATURE FRUIT 6 [hp_X]/1 mL; PULSATILLA PRATENSIS WHOLE 6 [hp_X]/1 mL; SUS SCROFA BILE DUCT 8 [hp_X]/1 mL; SUS SCROFA COLON 8 [hp_X]/1 mL; SUS SCROFA DUODENUM 8 [hp_X]/1 mL; SUS SCROFA ESOPHAGUS 8 [hp_X]/1 mL; SUS SCROFA EYE 8 [hp_X]/1 mL; SUS SCROFA GALLBLADDER 8 [hp_X]/1 mL; SUS SCROFA ILEUM 8 [hp_X]/1 mL; PORK INTESTINE 8 [hp_X]/1 mL; IPECAC 8 [hp_X]/1 mL; SUS SCROFA JEJUNUM 8 [hp_X]/1 mL; POTASSIUM DICHROMATE 8 [hp_X]/1 mL; SUS SCROFA LUNG 8 [hp_X]/1 mL; SUS SCROFA NASAL MUCOSA 8 [hp_X]/1 mL; SODIUM DIETHYL OXALACETATE 8 [hp_X]/1 mL; SUS SCROFA ORAL MUCOSA 8 [hp_X]/1 mL; SUS SCROFA PANCREAS 8 [hp_X]/1 mL; PHOSPHORUS 8 [hp_X]/1 mL; SUS SCROFA RECTAL MUCOSA 8 [hp_X]/1 mL; SUS SCROFA STOMACH 8 [hp_X]/1 mL; SULFUR 8 [hp_X]/1 mL; VERATRUM ALBUM ROOT 8 [hp_X]/1 mL; MANNOSE, D- 8 [hp_X]/1 mL; SEMECARPUS ANACARDIUM JUICE 9 [hp_X]/1 mL; WOOD CREOSOTE 10 [hp_X]/1 mL; LACHESIS MUTA VENOM 10 [hp_X]/1 mL; OXALIS ACETOSELLA LEAF 10 [hp_X]/1 mL; MANDRAGORA OFFICINARUM ROOT 16 [hp_X]/1 mL; SUS SCROFA URINARY BLADDER 6 [hp_C]/1 mL; SHIGELLA DYSENTERIAE 30 [hp_C]/1 mL
INACTIVE INGREDIENTS: WATER; ALCOHOL

DRUG FACTS:

ACTIVE INGREDIENTS:

Anacardium Orientale 9X, Argentum Nitricum 6X, Bile Duct (Suis) 8X, Ceanothus Americanus 4X, Colon (Suis) 8X, Condurango 6X, Duodenum (Suis) 8X, Dysentery Bacillus 30C, 200C, Esophagus (Suis) 8X, Eye (Suis) 8X, Gallbladder (Suis) 8X, Hydrastis Canadensis 6X, Ileum (Suis) 8X, Intestine (Suis) 8X, Ipecacuanha 8X, Jejunum (Suis) 8X, Kali Bichromicum 8X, Kreosotum 10X, Lachesis Mutus 10X, Lung (Suis) 8X, Mandragora Officinarum 16X, Mannose 8X, 30X, 200X, Momordica Balsamina 6X, Mucosa Nasalis Suis 8X, Natrum Oxalaceticum 8X, Oral Mucosa (Suis) 8X, Oxalis Acetosella 10X, Pancreas Suis 8X, Phosphorus 8X, Pulsatilla (Pratensis) 6X, Rectal Mucosa (Suis) 8X, Stomach (Suis) 8X, Sulphur 8X, Urinary Bladder (Suis) 6C, Veratrum Album 8X.

PURPOSE:

Anacardium Orientale – Occasional Diarrhea, Argentum Nitricum – Occasional Constipation, Bile Duct (Suis) – Irritated Eyes, Ceanothus Americanus - Headache, Colon (Suis) – Occasional Constipation, Condurango - Indigestion, Duodenum (Suis) - Gas, Dysentery Bacillus - Congestion, Esophagus (Suis) - Indigestion, Eye (Suis) – Irritated Eyes, Gallbladder (Suis) - Indigestion, Hydrastis Canadensis – Occasional Diarrhea, Ileum (Suis) – Occasional Diarrhea, Intestine (Suis) – Occasional Constipation, Ipecacuanha - Headache, Jejunum (Suis) – Occasional Constipation, Kali Bichromicum - Gas, Kreosotum – Irritated Eyes, Lachesis Mutus - Congestion, Lung (Suis) - Congestion, Mandragora Officinarum - Indigestion, Mannose – Occasional Diarrhea, Momordica Balsamina - Headache, Mucosa Nasalis Suis – Occasional Constipation, Natrum Oxalaceticum - Gas, Oral Mucosa (Suis) - Indigestion, Oxalis Acetosella - Gas, Pancreas Suis – Occasional Constipation, Phosphorus - Headache, Pulsatilla (Pratensis) - Gas, Rectal Mucosa (Suis) – Occasional Diarrhea, Stomach (Suis) - Indigestion, Sulphur – Irritated Eyes, Urinary Bladder (Suis) – Bladder Support, Veratrum Album – Occasional Constipation

USES:

• For the temporary relief of symptoms including:

• occasional diarrhea

• occasional constipation

• headache • gas • congestion

• irritated eyes • indigestion

• bladder support

These statements are based upon homeopathic principles. They have not been reviewed by the Food and Drug Administration.

WARNINGS:

If pregnant or breast-feeding, ask a health professional before use.

Keep out of reach of children. In case of overdose, contact a physician or Poison Control Center right away.

Tamper Evident: Sealed for your protection. Do not use if seal is broken or missing.

KEEP OUT OF REACH OF CHILDREN:

In case of overdose, contact a physician or Poison Control Center right away.

DIRECTIONS:

1-10 drops under the tongue, 3 times a day or as directed by a health professional. Consult a physician for use in children under 12 years of age.

INACTIVE INGREDIENTS:

Demineralized water, 25% ethanol

QUESTIONS:

Dist. By: Deseret Biologicals, Inc.
469 W. Parkland Drive
Sandy, UT 84070

www.desbio.com

800-827-8204

PACKAGE LABEL DISPLAY:

Des Bio

Matrix Support

Homeopathic
NDC 43742-1664-1

1 FL OZ (30 ml